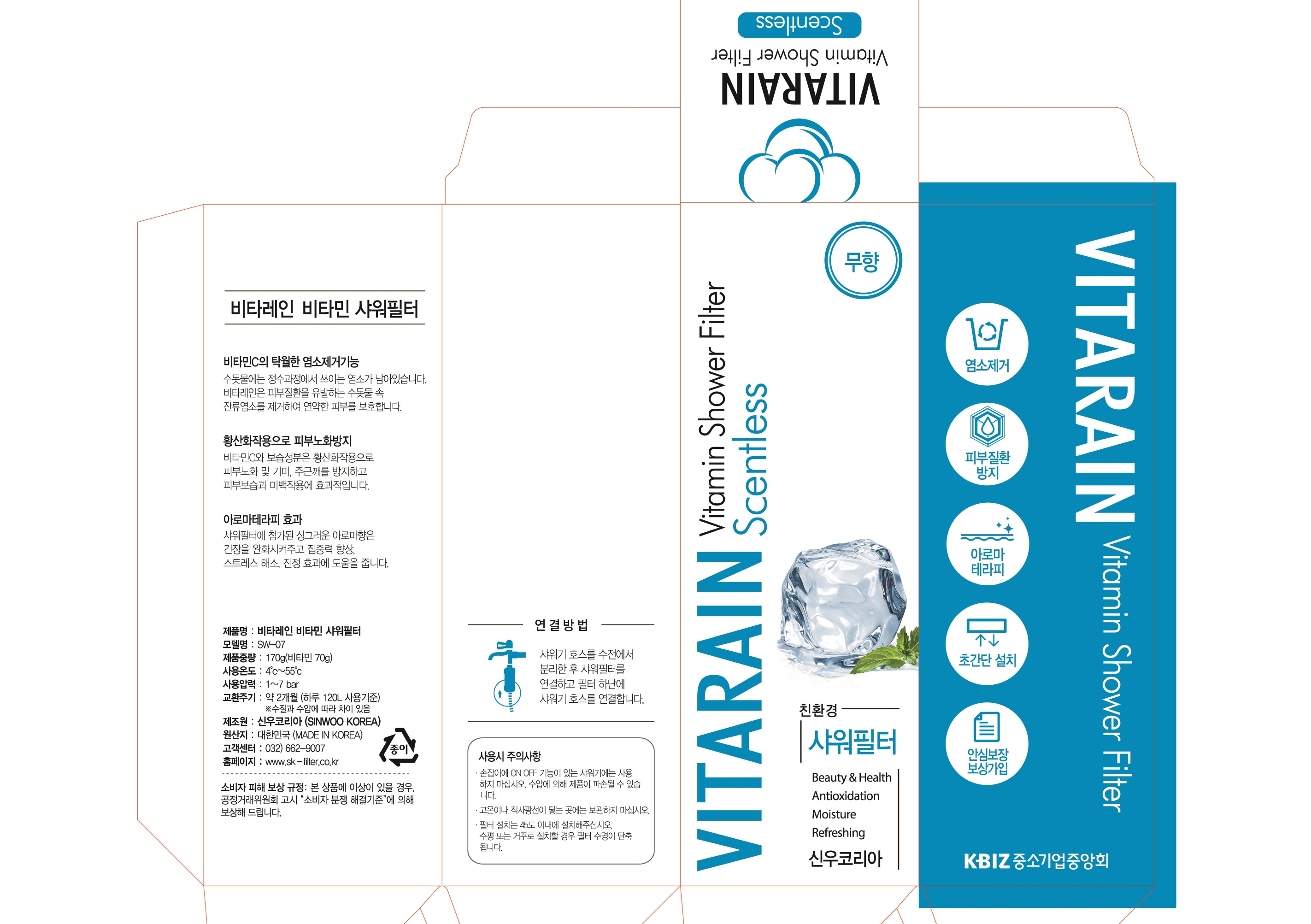 DRUG LABEL: VITARAIN VITAMIN SHOWER FILTER
NDC: 72538-0001 | Form: LIQUID
Manufacturer: Shinwoo Korea Co., Ltd.
Category: otc | Type: HUMAN OTC DRUG LABEL
Date: 20180830

ACTIVE INGREDIENTS: ASCORBIC ACID 36 g/70 g
INACTIVE INGREDIENTS: HONEY; GLYCERIN

Drug Facts

ACTIVE INGREDIENT

Ascorbic Acid

INACTIVE INGREDIENT

Dextrin, Keltrol, Glycerin, Nonfat Dry Milk, Food Coloring, Honey, Propolis, Perfume

PURPOSE

Skin Protectant

keep out of reach of the children

INDICATIONS AND USAGE

Remove the shower hose from the faucet, connect the shower filter, and connect the shower hose to the bottom of the filter.

WARNINGS

Precautions

1. If the cosmetic causes red rash, swollenness or itching by exposure to sunlight during the use, you are advised to stop using it immediately and you may consult a pharmacist or a doctor

2. It is not advised to use the cosmetic on the skin where you have scars

3. Precautions for storage

ⓐ Keep it out of infants or children’s reach

ⓑ Keep it out of the place where exposure to direct sunlight exists

DOSAGE AND ADMINISTRATION

for external use only